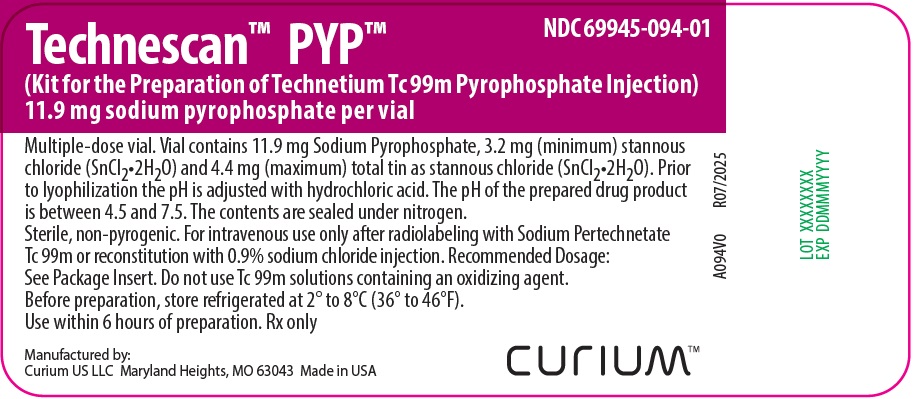 DRUG LABEL: Technescan PYP
NDC: 69945-094 | Form: INJECTION, POWDER, LYOPHILIZED, FOR SOLUTION
Manufacturer: Curium US LLC
Category: prescription | Type: HUMAN PRESCRIPTION DRUG LABEL
Date: 20251205

ACTIVE INGREDIENTS: SODIUM PYROPHOSPHATE 11.9 mg/10 mL; STANNOUS CHLORIDE 3.2 mg/10 mL
INACTIVE INGREDIENTS: HYDROCHLORIC ACID

Technescan™ PYP™
(Kit for the Preparation of Technetium Tc 99m Pyrophosphate Injection)
For Intravenous Use

DESCRIPTION

Drug Characteristics
Technescan™ PYP™ (kit for the preparation of technetium Tc 99m pyrophosphate injection) is a radioactive diagnostic drug for intravenous use after radiolabeling with sodium pertechnetate Tc 99m injection or after reconstitution with 0.9% sodium chloride injection in conjunction with sodium pertechnetate Tc 99m injection.

Each vial contains 11.9 mg sodium pyrophosphate, 3.2 mg (minimum) stannous chloride (SnCl2•2H2O), and 4.4 mg (maximum) total tin expressed as stannous chloride (SnCl2•2H2O). Prior to lyophilization, the pH is adjusted with hydrochloric acid. The pH of the reconstituted drug is between 4.5 and 7.5. No bacteriostatic preservative is present. The vial contains a sterile, non-pyrogenic, lyophilized powder packaged under nitrogen.

The precise structures of the stannous-pyrophosphate and technetium Tc 99m pyrophosphate complexes are not known.

Nuclear Physical Characteristics

Technetium-99m decays by isomeric transition with a physical half-life of 6.02 hours. The principal photon that is useful for detection and imaging is listed in Table 1.

Table 1. Principal Radiation Emission Data
Radiation | Mean % per Disintegration | Energy (keV)
Gamma-2 | 89.07 | 140.5

The specific gamma ray constant for technetium-99m is 0.795 R/hr-mCi at 1 cm. The first half-value layer is 0.023 cm of lead (Pb). A range of values for the relative attenuation of the radiation emitted by this radionuclide that results from interposition of various thicknesses of Pb is shown in Table 2. For example, the use of 0.27 cm thickness of Pb will attenuate the external radiation emitted by a factor of about 1,000.

Table 2. Radiation Attenuation by Lead Shielding
Shield Thickness (Pb) cm | Coefficient of Attenuation
0.023 0.09 0.18 0.27 | 0.5 10^-1 10^-2 10^-3

To correct for physical decay of this radionuclide, the fractions that remain at selected time intervals after the time of calibration are shown in Table 3.

Table 3. Physical Decay Chart; Technetium-99m, Half-Life 6.02 Hours
Hours | Fraction Remaining | Hours | Fraction Remaining
0* | 1 | 7 | 0.447
1 | 0.891 | 8 | 0.398
2 | 0.794 | 9 | 0.355
3 | 0.708 | 10 | 0.316
4 | 0.631 | 11 | 0.282
5 | 0.562 | 12 | 0.251
6 | 0.501
*Calibration Time

CLINICAL PHARMACOLOGY

Skeletal and Cardiac Imaging
When injected intravenously, technetium Tc 99m pyrophosphate has a specific affinity for areas of altered osteogenesis. It is also concentrated in the injured myocardium, primarily in areas of irreversibly damaged myocardial cells.

One to 2 hours after intravenous injection of technetium Tc 99m pyrophosphate, an estimated 40% to 50% of the injected dose is taken up by the skeleton, and approximately 0.01% to 0.02% of the injected dose is taken up per gram of acutely infarcted myocardium. Within a period of 1 hour, 10% to 11% remains in the vascular system, declining to approximately 2% to 3% 24 hours after injection. The average urinary excretion is approximately 40% of the administered dose after 24 hours.

Gated Cardiac Blood Pool and Gastrointestinal Bleed Imaging
Technescan PYP also has an affinity for red blood cells. When Technescan PYP reconstituted in 0.9% sodium chloride injection is administered 15 minutes to 30 minutes prior to the intravenous administration of sodium pertechnetate Tc 99m injection for red blood cell labeling, approximately 75% of the administered activity remains in the blood pool to allow imaging of the cardiac chambers. When the modified in vivo/in vitro red blood cell labeling method is used, comparable percentages of the injected radioactivity are obtained.

INDICATIONS AND USAGE

Technescan PYP, after radiolabeling with sodium pertechnetate Tc 99m, is indicated for:
• Skeletal imaging to demonstrate areas of altered osteogenesis in adults
• Cardiac imaging as an adjunct in the diagnosis of acute myocardial infarction in adults (See WARNINGS)

Technescan PYP, in conjunction with sodium pertechnetate Tc 99m injection for red blood cell (RBC) labeling, is indicated for gated cardiac blood pool imaging and for the detection of gastrointestinal bleeding sites in adults.

CONTRAINDICATIONS

None known.

WARNINGS

Image interpretation errors can occur. As an adjunct in the diagnosis of confirmed myocardial infarction (ECG and serum enzymes positive), the estimate of false negative image interpretations was 6%. False negative image interpretations can occur if made too early in the evolutionary phase of the infarct or too late in the resolution phase. In a study involving 22 patients in whom ECG was positive and serum enzymes questionable or negative, but in whom the final diagnosis of acute myocardial infarction was made, the estimates of false negative and false positive image interpretations were 23% and 9%, respectively. False positive image interpretations have been reported following coronary artery bypass graft surgery and in unstable angina pectoris, old myocardial infarcts, and cardiac contusions.

Technetium Tc 99m pyrophosphate may impair brain imaging with sodium pertechnetate Tc 99m and result in false positive or false negative image interpretation. It is recommended, where feasible, that brain imaging precede skeletal imaging procedures.

Gated cardiac blood pool and gastrointestinal bleed imaging may be impaired in patients receiving sodium heparin for anticoagulant therapy. This is characterized by a reduction in the amount of injected radioactivity remaining in the blood pool. Avoid heparinized catheter systems for administration of Technescan PYP.

The biodistribution of technetium Tc 99m pyrophosphate may be altered in the presence of high levels of certain cations (iron, calcium, and aluminum). This may result in reduced uptake of radionuclide in the skeleton and increased extraosseal uptake, which may potentially degrade imaging quality. High levels of these cations may be caused by concomitant medications or medical conditions (e.g., iron overload, hypercalcemia, etc.). Most cases are observed after iron infusion. (See PRECAUTIONS, Drug Interactions.)

PRECAUTIONS

General

Technetium Tc 99m pyrophosphate contributes to a patient’s overall long-term cumulative radiation exposure. Long-term cumulative radiation exposure is associated with an increased risk of cancer. Ensure safe drug handling to protect patients and healthcare providers from unintentional radiation exposure. (See DOSAGE AND ADMINISTRATION, Radiation Safety-Drug Handling.) Advise patients to drink fluids before and after administration and to void as often as possible after administration to reduce unnecessary exposure to radiation.

Drug Interactions

The biodistribution of technetium Tc 99m pyrophosphate may be altered in the presence of high levels of certain cations (iron, calcium, and aluminum). This may result in reduced uptake of radionuclide in the skeleton and increased extraosseal uptake, which may potentially degrade imaging quality. In patients with high levels of these cations caused by concomitant medications, particularly patients receiving iron infusions, consider performing an imaging study with technetium Tc 99m pyrophosphate injection once the cation levels have normalized (e.g., after 3 to 5 half-lives of the cation). (See WARNINGS.)

Carcinogenesis, Mutagenesis, Impairment of Fertility

No long-term animal studies have been performed to evaluate carcinogenic or mutagenic potential, or whether this drug affects fertility in males or females.

Pregnancy

Animal reproduction studies have not been conducted with Technetium Tc 99m Pyrophosphate Injection. It is also not known whether this drug can cause fetal harm when administered to a pregnant woman or can affect reproduction capacity.

All radiopharmaceuticals, including Technescan PYP, have the potential to cause fetal harm depending on the fetal stage of development and the magnitude of the radiation dose. If considering Technescan PYP administration to a pregnant woman, inform the patient about the potential for adverse pregnancy outcomes based on the radiation dose from technetium Tc 99m pyrophosphate and the gestational timing of exposure.

Nursing Mothers

Technetium-99m is excreted in human milk during lactation, therefore, formula feedings should be substituted for breast feeding.

Pediatric Use

Safety and effectiveness in pediatric patients have not been established.

Geriatric Use

Of the 137 subjects included in clinical studies of Technescan PYP labeled with technetium-99m for skeletal imaging, 28 subjects (20%) were 65 to 74 years of age, and 21 (15%) were 75 years of age and older. No overall differences in safety or effectiveness were observed between these subjects and younger subjects, and other reported clinical experience has not identified differences between elderly and younger patients.

This drug is known to be substantially excreted by the kidney, and the risk of toxic reactions to this drug may be greater in patients with impaired renal function. Because elderly patients are more likely to have decreased renal function, care should be taken in dose selection, and it may be useful to monitor renal function.

ADVERSE REACTIONS

The following adverse reactions associated with the use of Technescan PYP have been reported: flushing, hypotension, fever, chills, nausea, vomiting, and dizziness, as well as hypersensitivity reactions such as itching and various skin rashes.

OVERDOSAGE

In case of overdose of Technetium Tc 99m Pyrophosphate Injection, encourage patients to maintain hydration and to void frequently to minimize radiation exposure.

DOSAGE AND ADMINISTRATION

Radiation Safety – Drug Handling

After radiolabeling of Technescan PYP, the reaction vial contains Technetium Tc 99m Pyrophosphate Injection. Handle Technetium Tc 99m Pyrophosphate Injection with appropriate safety measures to minimize radiation exposure. (See PRECAUTIONS, General.) Use waterproof gloves, effective radiation shielding, and other appropriate safety measures when preparing and handling Technetium Tc 99m Pyrophosphate Injection.

Radiopharmaceuticals should be used by or under the control of healthcare providers who are qualified by specific training and experience in the safe use and handling of radionuclides, and whose experience and training have been approved by the appropriate governmental agency authorized to license the use of radionuclides.

Recommended Dosage, Administration, and Imaging Instructions for Skeletal and Cardiac Imaging

Dosing and Administration Instructions

- The recommended activity of Technetium Tc 99m Pyrophosphate Injection for each type of imaging is presented in Table 4.
- Administer Technetium Tc 99m Pyrophosphate Injection intravenously over 10 seconds to 20 seconds.
- Measure the patient dose with a dose calibrator immediately before administration.
- If not contraindicated by patient’s condition, encourage patients to drink fluids before and after administration and void as often as possible to reduce unnecessary radiation exposure.
- For radiolabeling instructions, see Directions for Drug Preparation, Procedure for the Preparation of Technetium Tc 99m Pyrophosphate Injection.

Table 4. Recommended Administered Activity of Technetium Tc 99m Pyrophosphate Injection for Skeletal and Cardiac Imaging in Adults

Indication | Activity of Technetium Tc 99m Pyrophosphate | Fraction of Vial Contents Required for Pyrophosphate
Skeletal Imaging | 185 MBq to 555 MBq (5 mCi to 15 mCi) | 0.07 to 0.91
Cardiac Imaging | 370 MBq to 555 MBq (10 mCi to 15 mCi) | 0.26 to 0.45

Skeletal Imaging
Begin imaging 1 hour to 6 hours following administration.

Cardiac Imaging

- The patient's cardiac condition should be stable before beginning the cardiac imaging procedure.
- Begin imaging 60 minutes to 90 minutes following administration. The acute myocardial infarct can be visualized from 24 hours to 9 days following onset of symptoms, with maximum localization at 48 to 72 hours. Cardiac imaging should be done with a gamma scintillation camera. It is recommended that images include anterior, left anterior oblique, and left lateral projections.
- Interference from chest wall lesions such as breast tumors and healing rib fractures can be minimized by employing the three recommended projections.

Recommended Dosage, Administration, and Imaging Instructions for Gated Cardiac Blood Pool and Gastrointestinal Bleed Imaging

Dose
The recommended dose of Technescan PYP reconstituted in 0.9% sodium chloride injection for gated cardiac blood pool and gastrointestinal bleed imaging in adults is 1 mL, followed by 555 MBq to 740 MBq (15 mCi to 20 mCi) of sodium pertechnetate Tc 99m injection.

Administration Instructions for In Vivo RBC Labeling Method

a. Reconstitute Technescan PYP with 0.9% sodium chloride injection. (See Directions for Drug Preparation, Procedure for the Reconstitution of Technescan PYP.)

b. Administer the patient dose of reconstituted Technescan PYP intravenously by direct venipuncture. Do not use heparinized catheters. (See WARNINGS.)

c. Wait 15 minutes to 30 minutes.

d. Administer sodium pertechnetate Tc 99m injection intravenously.

Administration Instructions for Modified In Vivo/In Vitro RBC Labeling Method Using ACD

a. Reconstitute Technescan PYP with 0.9% sodium chloride injection. (See Directions for Drug Preparation, Procedure for the Reconstitution of Technescan PYP.)

b. Administer the patient dose of reconstituted Technescan PYP intravenously by direct venipuncture. Do not use heparinized catheters. (See WARNINGS.)

c. Insert an intravenous line with a 3-way stopcock in a large peripheral vein and maintain the line with a continuous drip of 0.9% sodium chloride injection.

d. 30 minutes post-injection:

- Clear the line by withdrawing and discarding approximately 5 mL of blood.
- Then draw approximately 5 mL of blood into a syringe containing 1 mL preservative-free acid-citrate-dextrose (ACD) and 555 MBq to 740 MBq (15 mCi to 20 mCi) of sodium pertechnetate Tc 99m injection.
- Turn the stopcock, flush the line, and adjust the flow of 0.9% sodium chloride injection.

e. Gently rotate syringe to mix and incubate at room temperature for 10 minutes.

f. Inject the mixture via the 3-way stopcock.

Administration Instructions for Modified In Vivo/In Vitro RBC Labeling Method Using Heparin

a. Reconstitute Technescan PYP with 0.9% sodium chloride injection. (See Directions for Drug Preparation, Procedure for the Reconstitution of Technescan PYP.)

b. Administer the patient dose of reconstituted Technescan PYP intravenously by direct venipuncture. Do not use heparinized catheters. (See WARNINGS.)

c. Insert an infusion set fitted with a 3-way stopcock in a large peripheral vein, and heparinize the intravenous line with 0.9% sodium chloride injection containing 5 units/mL to 10 units/mL of preservative-free heparin.

d. Thirty minutes after Technescan PYP injection, draw 3 mL of blood into a syringe containing 555 MBq to 740 MBq (15 mCi to 20 mCi) of sodium pertechnetate Tc 99m injection. Anticoagulation of the blood is provided by residual heparin in the intravenous line.

e. Gently rotate the syringe to mix and incubate at room temperature for 10 minutes.

f. Inject the mixture via the 3-way stopcock.

Gated Cardiac Blood Pool Imaging
Begin cardiac imaging 10 minutes following the administration of sodium pertechnetate Tc 99m injection (in vivo method) or Tc 99m labeled red blood cells (modified in vivo/in vitro method) utilizing a scintillation camera interfaced to an electrocardiographic gating device.

Gastrointestinal Bleed Imaging
The imaging of gastrointestinal bleeding is dependent on factors such as the region of imaging, rate and volume of the bleed, efficacy of labeling of the red blood cells, and timeliness of imaging. Acquire sequential images over a period of time until a positive image is obtained or clinical conditions warrant the discontinuance of the procedure. The period of time for collecting the images may range up to 36 hours.

Directions for Drug Preparation

Procedural Precautions

• The contents of the Technescan PYP reaction vial may be used for the preparation of Technetium Tc 99m Pyrophosphate Injection. Technescan PYP may also be reconstituted with preservative-free 0.9% sodium chloride injection and injected intravenously prior to labeling of red blood cells with sodium pertechnetate Tc 99m injection using either the in vivo or modified in vivo/in vitro method.

• The components of the kit are sterile and non-pyrogenic. It is essential that the user follow the directions carefully and adhere to strict aseptic procedures during preparation.

• Wear waterproof gloves during the entire preparation procedure and during subsequent patient dose withdrawals from the reaction vial.

• Make all withdrawals and administration of sodium pertechnetate Tc 99m injection with an adequately shielded syringe.

• Keep the prepared Technetium Tc 99m Pyrophosphate Injection in the lead shield described below (with cap in place) during the useful life of the radioactive preparation. Make all withdrawals and administration of the Technetium Tc 99m Pyrophosphate Injection with an adequately shielded syringe.

• Any sodium pertechnetate Tc 99m injection that contains an oxidizing agent is not suitable for use in the preparation of Technetium Tc 99m Pyrophosphate Injection.

Procedure for the Preparation of Technetium Tc 99m Pyrophosphate Injection

1. Remove a Technescan PYP reaction vial from the refrigerator and allow the vial contents to come to room temperature, 20°C to 25°C (68°F to 77°F), for approximately 5 minutes.

2. Attach the radioassay information label with radiation warning symbol to the reaction vial and place the vial in a lead Dispensing Shield fitted with a lead cap and having a minimum wall thickness of 1/8 inch. Do not remove the reaction vial from the Dispensing Shield, except temporarily, for Step 5 below.

3. Add 1 mL to 10 mL of sodium pertechnetate Tc 99m injection to the reaction vial. In choosing the amount of the sodium pertechnetate Tc 99m injection radioactivity to be used in the preparation of the Technetium Tc 99m Pyrophosphate Injection, the labeling efficiency, number of patients, administered radioactive dose, and radioactive decay must be taken into account. The recommended maximum activity of sodium pertechnetate Tc 99m injection to be added to the reaction vial is 3,700 MBq (100 mCi).

4. With the reaction vial in the Dispensing Shield (with cap in place), shake sufficiently to bring the lyophilized material into solution. Allow to stand for 5 minutes at room temperature.

5. Using proper shielding, visually inspect the reaction vial. The resulting solution should be clear and free of particulate matter. If not, do not use the product.

6. Assay the product in a suitable calibrator and record the time, date of preparation, and the activity of the Technetium Tc 99m Pyrophosphate Injection onto the radioassay information label.

7. Check the radiochemical purity prior to administration.

8. Store the reaction vial in the Dispensing Shield at 20°C to 25°C (68° to 77°F). Use within 6 hours of radiolabeling.

9. Dispose of unused drug in a safe manner in accordance with applicable regulations.

Procedure for the Reconstitution of Technescan PYP

a. Remove a Technescan PYP reaction vial from the refrigerator and allow the vial contents to come to room temperature, 20°C to 25°C (68°F to 77°F), for approximately 5 minutes.

b. Add 3 mL of preservative-free 0.9% sodium chloride injection to the reaction vial.

c. Shake the reaction vial sufficiently to bring the lyophilized material into solution. Allow to stand for 5 minutes at room temperature.

d. Visually inspect the reaction vial. The resulting solution should be clear and free of particulate matter. If not, do not use the product.

e. Store the reconstituted reaction vial upright at 20°C to 25°C (68°F to 77°F). Use within 6 hours of reconstitution.

Radiation Dosimetry

Skeletal and Cardiac Imaging

Estimated absorbed radiation doses from an intravenous injection of Technetium Tc 99m Pyrophosphate Injection in adults are shown in Table 5.

Table 5. Estimated Absorbed Radiation Doses in Organs and Tissues in Adults Who Received Technetium Tc 99m Pyrophosphate Injection
Organ/Tissue | Absorbed Dose per Unit Activity Administered (mGy/MBq)
Skeleton* | 0.010
Bone Marrow | 0.008
Kidneys | 0.038
Total Body | 0.002
Bladder
2-hr. void | 0.026
4.8-hr. void | 0.062
Testes
2-hr. void | 0.003
4.8-hr. void | 0.004
Ovaries
2-hr. void | 0.003
4.8-hr. void | 0.004
Heart
Normal | 0.002
Impaired | 0.004

*Dose at point of highest uptake may be a factor of 10 higher.

Gated Cardiac Blood Pool and Gastrointestinal Bleed Imaging
Estimated absorbed radiation doses from an intravenous administration of sodium pertechnetate Tc 99m injection, 30 minutes after the intravenous administration of Technescan PYP are shown in Table 6.

Table 6. Estimated Absorbed Radiation Doses in Adults Who Received Sodium Pertechnetate Tc 99m Injection 30 minutes after Technescan PYP Administration*
Organ/Tissue | Absorbed Dose per Unit Activity Administered (mGy/MBq)
Bladder Wall | 0.009
Ovaries | 0.006
Testes | 0.004
Red Marrow | 0.005
Spleen** | 0.004
Blood | 0.014
Total Body | 0.004

*Assumes non-resting state, with 75% of the sodium pertechnetate Tc 99m labeling red blood cells and the other 25% remaining as pertechnetate.
**Assumes no initial uptake in spleen.

HOW SUPPLIED

Technescan PYP (kit for the preparation of technetium Tc 99m pyrophosphate injection) contains 11.9 mg sodium pyrophosphate as a white lyophilized powder in a multiple-dose vial.

Technescan PYP is available in cartons of 5 vials (NDC 69945-094-20).

Before preparation, store the Technescan PYP reaction vial refrigerated at 2°C to 8°C (36°F to 46°F).

After preparation, store the vial at 20°C to 25°C (68°F to 77°F) [see USP Controlled Room Temperature]. If radiolabeled, store the vial in appropriate shielding to protect from radiation. Use within 6 hours of preparation.

Dispose of unused Technetium Tc 99m Pyrophosphate Injection in accordance with appropriate regulations.

This reagent kit is for distribution to persons licensed by the U.S. Nuclear Regulatory Commission or the relevant regulatory authority of an Agreement State.

Manufactured by:
Curium US LLC
2703 Wagner Place
Maryland Heights, MO 63043

Made in USA

©2025 Curium US LLC. TechnescanTMPYPTM, CuriumTM, and the Curium logo are trademarks of a Curium company.

A094I0
Revised: 11/2025

CURIUM™

PRINCIPAL DISPLAY PANEL - A094V0

Technescan™ PYP™ NDC 69945-094-01

(Kit for the Preparation of Technetium Tc 99m Pyrophosphate Injection)

11.9 mg sodium pyrophosphate per vial

Multiple-dose vial. Vial contains 11.9 mg Sodium Pyrophosphate, 3.2 mg (minimum) stannous chloride (SnCl2•2H2O) and 4.4 mg (maximum) total tin as stannous chloride (SnCl2•2H2O). Prior to lyophilization the pH is adjusted with hydrochloric acid. The pH of the prepared drug product is between 4.5 and 7.5. The contents are sealed under nitrogen.
Sterile, non-pyrogenic. For intravenous use only after radiolabeling with Sodium Pertechnetate Tc 99m or reconstitution with 0.9% sodium chloride injection. Recommended Dosage: See Package Insert. Do not use Tc 99m solutions containing an oxidizing agent.
Before preparation, store refrigerated at 2° to 8°C (36° to 46°F).
Use within 6 hours of preparation. Rx only
Manufactured by:
Curium US LLC Maryland Heights, MO 63043 Made in USA

CURIUM™

A094V0 R07/2025